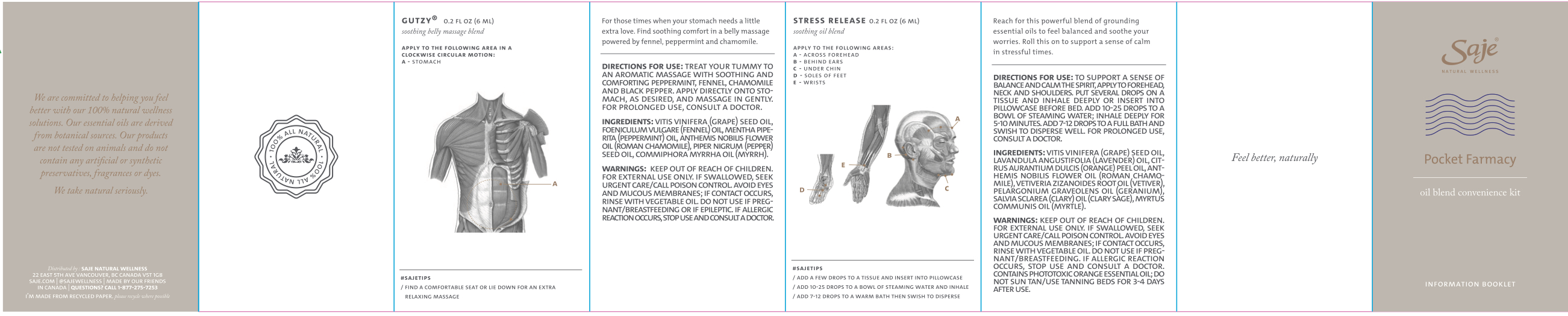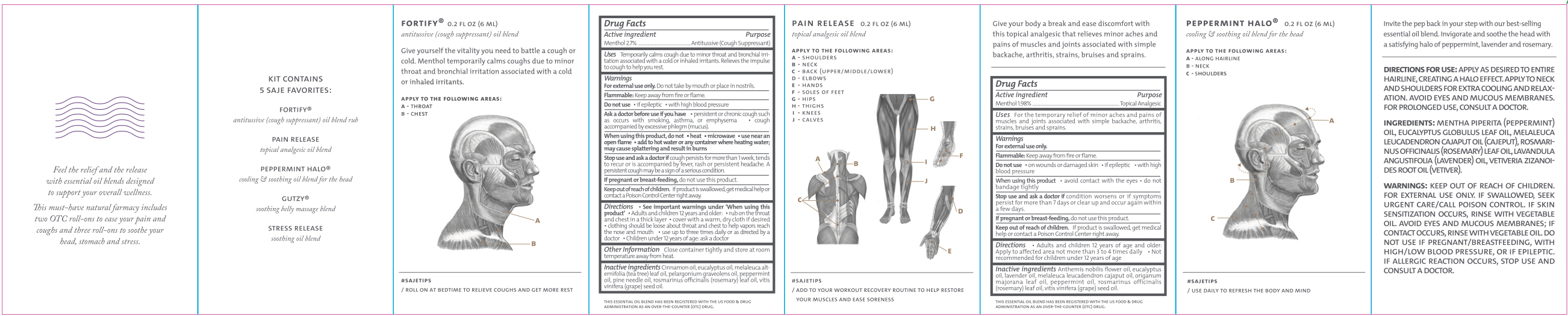 DRUG LABEL: Pocket Farmacy
NDC: 70983-013 | Form: KIT | Route: TOPICAL
Manufacturer: Saje Natural Business Inc.
Category: otc | Type: HUMAN OTC DRUG LABEL
Date: 20260114

ACTIVE INGREDIENTS: MENTHOL 24.03 mg/1 mL; MENTHOL 17.62 mg/1 mL
INACTIVE INGREDIENTS: CINNAMON OIL; EUCALYPTUS OIL; TEA TREE OIL; PELARGONIUM GRAVEOLENS FLOWER OIL; PEPPERMINT OIL; PINE NEEDLE OIL (PINUS SYLVESTRIS); ROSEMARY OIL; GRAPE SEED OIL; CHAMAEMELUM NOBILE FLOWER OIL; EUCALYPTUS OIL; LAVENDER OIL; CAJUPUT OIL; SWEET MARJORAM OIL; PEPPERMINT OIL; ROSEMARY OIL; GRAPE SEED OIL

Pocket Farmacy Oil Blend Convenience Kit

FORTIFY antitussive (cough suppressant) oil blend rub Drug Facts Active ingredient

Menthol 2.7%

Take this convenient pouch with you everywhere you go to enjoy Saje's best-selling oil blends whenever you need them. Combat everyday challenges and enhance your day, naturally.

Kit Contains 5 Saje Best-Sellers:

FORTIFY antitussive (cough suppressant) oil blend rub

PAIN RELEASE topical analgesic oil blend

peppermint halo COOLING & SOOTHING OIL BLEND FOR THE HEAD

gutzy SOOTHING BELLY MASSAGE BLEND

stress release SOOTHING OIL BLEND

IMPORTANT: FOR EACH PRODUCT, READ ALL PRODUCT INFORMATION ON OUTER AND INNER BOX FLAP BEFORE USING. KEEP THIS PACKAGE FOR FULL INFORMATION.

DO NOT USE IF SECURITY SEAL AROUND BOTTLES IS BROKEN OR MISSING.

Distributed by: SAJE NATURAL WELLNESS | 22 East 5th Ave Vancouver, BC Canada V5T 1G8 | saje.com | 1-877-275-7253 | Made by our friends in Canada

We support recycling. Please recycle where possible

SKU 22251201

Lift here for inner flap & important product information on all oil blends.

GET READY FOR WELLNESS

Purpose Antitussive (Cough Suppressant)

Uses Temporarily calms cough due to minor throat and bronchial irritation associated with a cold or inhaled irritants. Relieves the impulse to cough to help you rest.

Do not use

- if epileptic
- with high blood pressure

Warnings

For external use only.

Flammable. Keep away from fire or flame.

Ask doctor before use if you have

- persistent or chronic cough such as occurs with smoking, asthma, or emphysema
- cough accompanied by excessive phlegm (mucus)

When using this product, do not

- heat
- microwave
- use near an open flame
- add to hot water or any container where heating water. May cause splattering and result in burns.

Stop use and ask a doctor if

cough persists for more than 1 week, tends to recur, or is accompanied by fever, rash, or persistent headache. A persistent cough may be a sign of a serious condition.

If pregnant or breastfeeding,

do not use this product.

Keep out of reach of children.

If product is swallowed, get medical help or contact a Poison Control Center right away.

Directions

- See important warnings under 'when using this product'
- Adults and children 12 years and older:
- rub on throat and chest in a thick layer
- cover with a warm, dry cloth if desired
- clothing should be loose about throat and chest to help vapors reach the nose and mouth

DOSAGE AND ADMINISTRATION

- use up to three times daily or as directed by a doctor
- Children under 12 years: ask a doctor.

Other information

Close container tightly and store at room temperature away from heat.

Inactive ingredients

Cinnamon oil, eucalyptus oil, melaleuca alternifolia (tea tree) leaf oil, pelargonium graveolens oil, peppermint oil, pine needle oil, rosmarinus officinalis (rosemary) leaf oil, and vitis vinifera (grape) seed oil.

FORTIFY antitussive (cough suppressant) oil blend rub

Apply to the following areas, as directed:

A - Throat

B - Chest

PAIN RELEASE topical analgesic oil blend Drug Facts Active ingredient

Menthol 1.98%

Purpose Topical Analgesic

Uses For the temporary relief of minor aches and pains of muscles and joints associated with simple backache, arthritis, strains, bruises, and sprains

Warnings

For external use only.

Flammable. Keep away from fire or flame.

Do not use

- on wounds or damaged skin
- if epileptic
- with high blood pressure

When using this product,

- avoid contact with the eyes
- do not bandage tightly

Stop use and ask a doctor if

condition worsens, or if symptoms persist for more than 7 days or clear up and occur again within a few days.

If pregnant or breast-feeding,

do not use this product

Keep out of reach of children.

If product is swallowed, get medical help or contact a Poison Control Center right awa y.

Directions

- Adults and children 12 years of age and older: Apply to affected area

DOSAGE AND ADMINISTRATION

not more than 3 to 4 times daily

- Not recommended for children under 12 years of age

Inactive ingredients

Anthemis nobilis flower oil, eucalyptus oil, lavender oil, melaleuca leucadendron cajaput oil, origanum majorana leaf oil, peppermint oil, rosmarinus officinalis (rosemary) leaf oil, and vitis vinifera (grape) seed oil.

PAIN RELEASE topical analgesic oil blend

Apply to muscles & joints experiencing minor aches & pains, as directed:

A - Shoulders

B - Neck

C - Back (upper/middle/lower)

D - Elbows

E - Hands

F - Soles of Feet

G - Hips

H - Thighs

I - Knees

J - Calves

SOOTHING OIL BLENDS PEPPERMINT HALO cooling & soothing oil blend for the head

Apply to the following areas:

A - Along hairline

B - Neck

C - Shoulders

Directions for use: Apply as desired to entire hairline, creating a halo effect. Apply to neck and shoulders for extra cooling and relaxation. Avoid eyes and mucous membranes. For prolonged use, consult a doctor.

Ingredients: Mentha piperita (peppermint) oil, eucalyptus globulus leaf oil, melaleuca leucadendron cajaput oil, rosmarinus officinalis (rosemary) leaf oil, lavandula angustifolia (lavender) oil, and vetiveria zizanoides root oil.

Warnings:

- Keep out of reach of children.
- For external use only. if swallowed, seek urgent care/call poison control.
- If skin sensitization occurs, rinse with vegetable oil.
- Avoid eyes & mucous membranes; if contact occurs, rinse with vegetable oil.
- Do not use if pregnant/breastfeeding, with high/low blood pressure, or if epileptic.
- If allergic reaction occurs, stop use & consult a doctor.

GUTZY soothing belly massage blend

Apply to the following areas:

A - Stomach

Directions for use: Treat your tummy to an aromatic massage with soothing and comforting peppermint, fennel, chamomile, and black pepper. apply directly onto stomach, as desired, and massage in gently. For prolonged use, consult a doctor.

Ingredients: vitis vinifera (grape) seed oil, foeniculum vulgare (fennel) oil, mentha piperita (peppermint) oil, anthemis nobilis flower oil, piper nigrum (pepper) seed oil, and commiphora myrrha oil.

Warnings:

- Keep out of reach of children.
- For external use only. if swallowed, seek urgent care/call poison control.
- Avoid eyes & mucous membranes; if contact occurs, rinse with vegetable oil.
- Do not use if pregnant/breastfeeding or if epileptic.
- If allergic reaction occurs, stop use & consult a doctor.

STRESS RELEASE soothing oil blend

Apply to the following areas:

A - Forehead

B - Neck

C - Shoulders

Directions for use: To support a sense of balance & calm the spirit, apply to forehead, neck & shoulders. Put several drops on a tissue & inhale deeply or insert into pillowcase before bed. Add 10-25 drops to a bowl of steaming water; inhale deeply for 5-10 minutes. Add 7-12 drops to a full bath & swish to disperse well. For prolonged use, consult a doctor.

Ingredients: vitis vinifera (grape) seed oil, lavandula angustifolia (lavender) oil, citrus aurantium dulcis (orange) peel oil, anthemis nobilis flower oil, vetiveria zizanoides root oil, pelargonium graveolens oil, salvia sclarea (clary) oil, and myrtus communis oil.

Warnings:

- Keep out of reach of children.
- For external use only. if swallowed, seek urgent care/call poison control.
- Avoid eyes & mucous membranes; if contact occurs, rinse with vegetable oil.
- Do not use if pregnant/breastfeeding.
- If allergic reaction occurs, stop use & consult a doctor.
- Contains phototoxic orange essential oil; do not sun tan/use tanning beds for 3-4 days after use.

Saje is committed to providing 100% natural products containing pure essential oils and ingredients derived from mineral and botanical sources. Saje products are not tested on animals and do not contain any artificial or synthetic chemicals, preservatives, fragrances or colors.

RECENT MAJOR CHANGES

not more than 3 to 4 times daily

Not recommended for children under 12 years of age

PACKAGE LABEL

Saje® Natural Wellness

POCKET FARMACY

oil blend convenience kit

1 ANTITUSSIVE (COUGH SUPPRESSANT) OIL BLEND RUB 0.2 FL. OZ. | 6 mL

1 TOPICAL ANALGESIC OIL BLEND 0.2 FL. OZ. | 6 mL

3 OIL BLENDS X 0.2 FL. OZ. | 6 mL